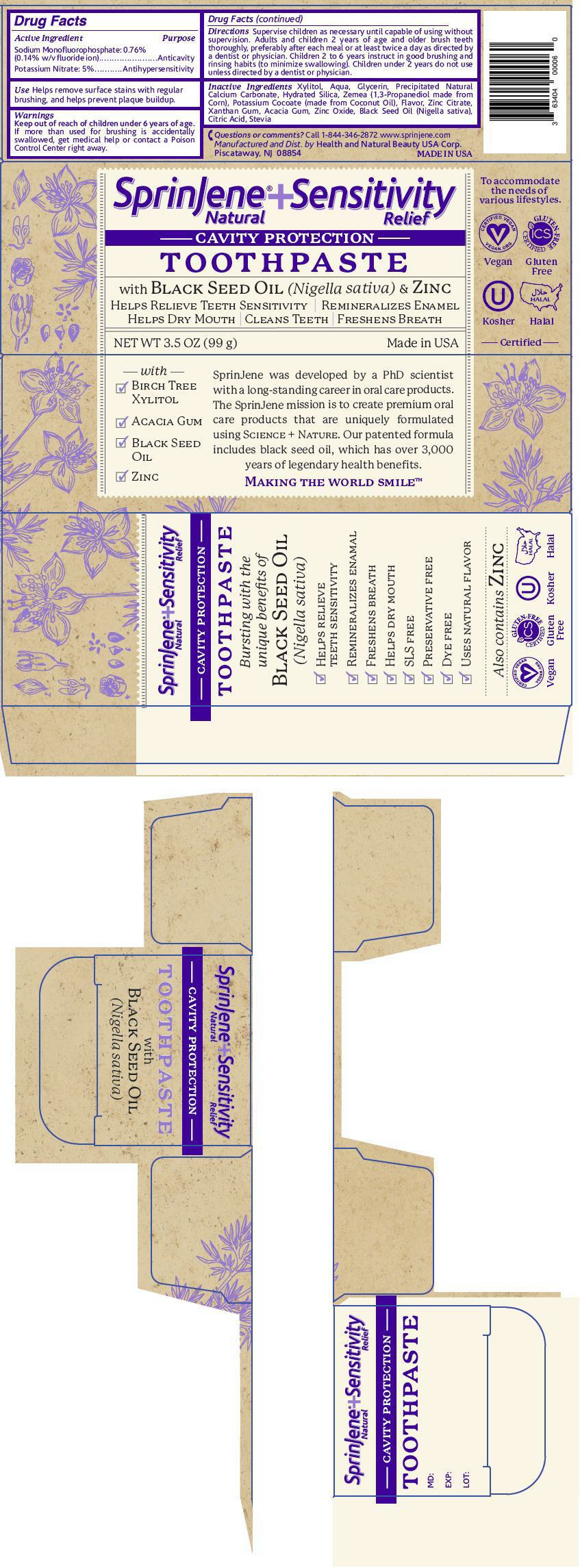 DRUG LABEL: SprinJene Natural 
NDC: 63404-1942 | Form: PASTE, DENTIFRICE
Manufacturer: Health and Natural Beauty USA Corp
Category: otc | Type: HUMAN OTC DRUG LABEL
Date: 20170905

ACTIVE INGREDIENTS: Sodium Monofluorophosphate 1.5 mg/1 g; Potassium Nitrate 50 mg/1 g
INACTIVE INGREDIENTS: Water; Glycerin; Calcium Carbonate; Silicon Dioxide; Propanediol; Potassium Cocoate; Zinc Citrate; Xanthan Gum; Acacia; Zinc Oxide; CITRIC ACID MONOHYDRATE; STEVIA REBAUDIUNA LEAF

SprinJene® Natural
Sensitivity Relief

Drug Facts

ACTIVE INGREDIENT

Active Ingredient | Purpose
Sodium Monofluorophosphate: 0.76% (0.14% w/v fluoride ion) | Anticavity
Potassium Nitrate: 5% | Antihypersensitivity

Use

Helps remove surface stains with regular brushing, and helps prevent plaque buildup.

Warnings

Keep out of reach of children under 6 years of age. If more than used for brushing is accidentally swallowed, get medical help or contact a Poison Control Center right away.

Directions

Supervise children as necessary until capable of using without supervision. Adults and children 2 years of age and older brush teeth thoroughly, preferably after each meal or at least twice a day as directed by a dentist or physician. Children 2 to 6 years instruct in good brushing and rinsing habits (to minimize swallowing). Children under 2 years do not use unless directed by a dentist or physician.

Inactive Ingredients

Xylitol, Aqua, Glycerin, Precipitated Natural Calcium Carbonate, Hydrated Silica, Zemea (1,3-Propanediol made from Corn), Potassium Cocoate (made from Coconut Oil), Flavor, Zinc Citrate, Xanthan Gum, Acacia Gum, Zinc Oxide, Black Seed Oil (Nigella sativa), Citric Acid, Stevia

Questions or comments?

Call 1-844-346-2872 www.sprinjene.com

Manufactured and Dist. by Health and Natural Beauty USA Corp.
Piscataway, NJ 08854

PRINCIPAL DISPLAY PANEL - 99 g Tube Carton

SprinJene®+Sensitivity
Natural
Relief

CAVITY PROTECTION

TOOTHPASTE

with Black Seed Oil (Nigella sativa) & Zinc
Helps Relieve Teeth Sensitivity | Remineralizes Enamel
Helps Dry Mouth | Cleans Teeth | Freshens Breath

NET WT 3.5 OZ (99 g)
Made in USA

To accommodate
the needs of
various lifestyles.

CERTIFIED VEGAN
V
VEGAN.ORG
Vegan

GLUTEN-FREE
ICS
CERTIFIED
Gluten
Free

U
Kosher

HALAL
Halal

Certified